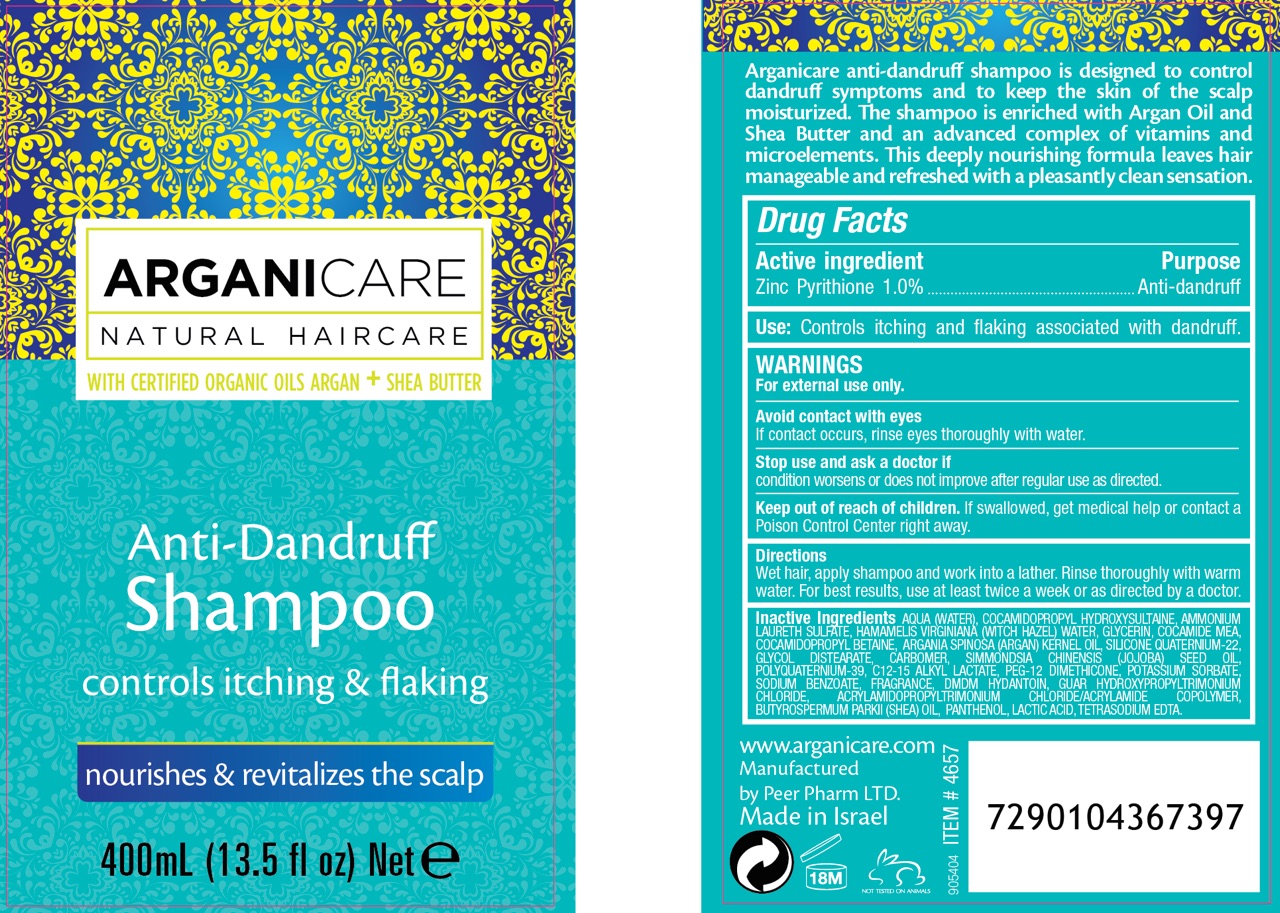 DRUG LABEL: AntiDandruffShampoo
NDC: 69435-1608 | Form: SHAMPOO
Manufacturer: Peer Pharm Ltd.
Category: otc | Type: HUMAN OTC DRUG LABEL
Date: 20160621

ACTIVE INGREDIENTS: PYRITHIONE ZINC 1 g/100 mL
INACTIVE INGREDIENTS: COCO MONOETHANOLAMIDE; GLYCOL DISTEARATE; PANTHENOL; WATER; AMMONIUM LAURETH-12 SULFATE; GLYCERIN; JOJOBA OIL; HAMAMELIS VIRGINIANA TOP WATER; COCAMIDOPROPYL BETAINE; POLYQUATERNIUM-39 (22.5/51/26.5 ACRYLIC ACID/ACRYLAMIDE/DADMAC; 1600000 MW); C12-15 ALKYL LACTATE; PEG-12 DIMETHICONE (300 CST); POTASSIUM SORBATE; DMDM HYDANTOIN; GUAR HYDROXYPROPYLTRIMONIUM CHLORIDE (1.7 SUBSTITUENTS PER SACCHARIDE); ACRYLAMIDOPROPYLTRIMONIUM CHLORIDE/ACRYLAMIDE COPOLYMER (400 MPA.S); SHEANUT OIL; LACTIC ACID; EDETATE SODIUM; SODIUM BENZOATE; COCAMIDOPROPYL HYDROXYSULTAINE; ARGAN OIL; CARBOMER 1342

Arganicare Anti-Dandruff Shampoo

PACKAGE LABEL

ACTIVE INGREDIENT

Zinc Pyrithione 1.0%

PURPOSE

Controls Dandruff

Keep out of reach of children.

INDICATIONS AND USAGE

Controls itching and flaking associated with dandruff

WARNINGS

For external use only. Avoid contact with eyes. If contact occurs, rinse eyes throughly with water. If condition worsens or does not improve after regular use of this product as directed, consult a doctor.

DOSAGE AND ADMINISTRATION

Wet hair, apply shampoo and work into a lather. Rinse thoroughly with warm water. For best results, use at least twice a week or as direct by a doctor.